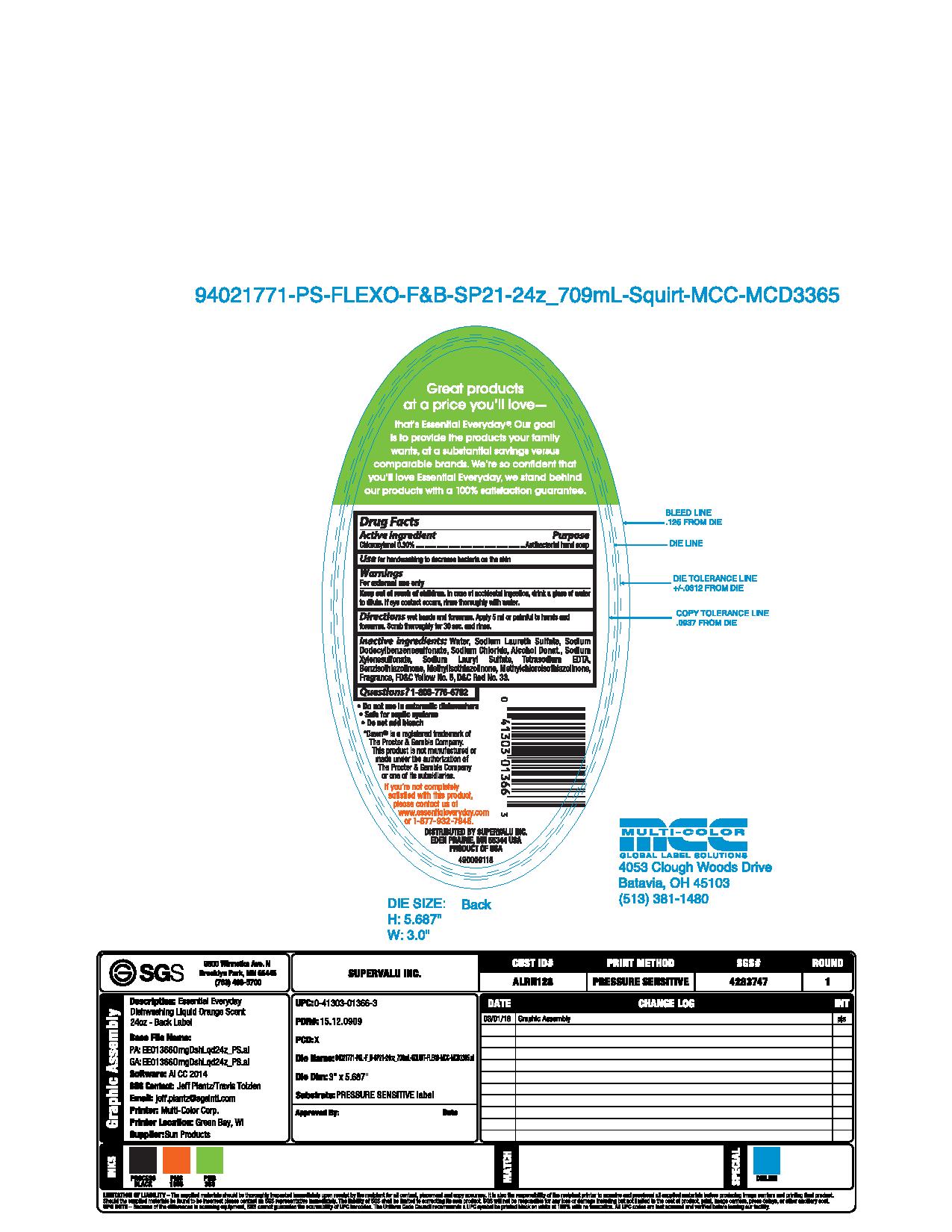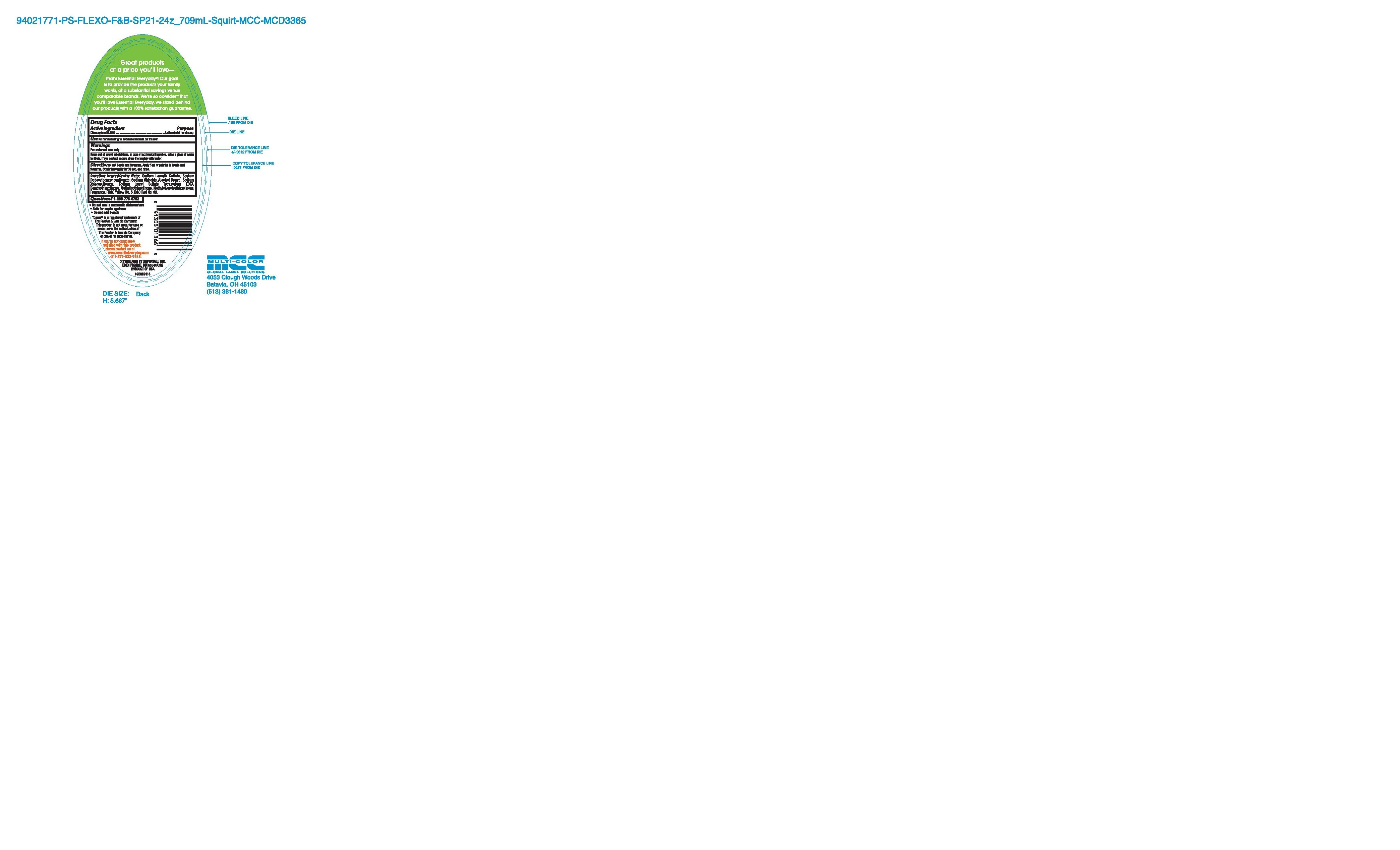 DRUG LABEL: Essential Everyday Dishwashing Liquid Orange
NDC: 63691-030 | Form: SOAP
Manufacturer: Sun Products Corporation
Category: otc | Type: HUMAN OTC DRUG LABEL
Date: 20160630

ACTIVE INGREDIENTS: CHLOROXYLENOL 0.3 g/100 mL
INACTIVE INGREDIENTS: ALCOHOL; SODIUM LAURYL SULFATE; SODIUM CHLORIDE; SODIUM XYLENESULFONATE; D&C RED NO. 33; METHYLCHLOROISOTHIAZOLINONE; SODIUM LAURETH SULFATE; WATER; SODIUM DODECYLBENZENESULFONATE; EDETATE SODIUM; BENZISOTHIAZOLINONE; METHYLISOTHIAZOLINONE; FD&C YELLOW NO. 5

Active Ingredient

Chloroxylenol 0.30%

Purpose

Antibacterial hand soap

Use

for handwashing to decrease bacteria on the skin

Warnings

For external use only

Keep out of reach of children.

In case of accidental ingestion, drink a glass of water to dilute. If eye contact occurs, rinse thoroughly with water.

Directions

wet hands and forearms. Apply 5 ml or palmful to hands and forearms. Scrub thoroughly for 30 sec. and rinse.

Inactive Ingredients:

Water, Sodium Laureth Sulfate, Sodium Dodecybenzenesulfonate, Sodium Chloride, Alcohol Denat., Sodium Xylenesulfonate, Sodium Lauryl Sulfate, Tetrasodium EDTA, Benzisothiazolinone, Methyisothiazolinone, Methylchloroisothiazolinone, Fragrance, FD&C Yellow No. 5, D&C Red No. 33

Questions?

1-800-776-6702